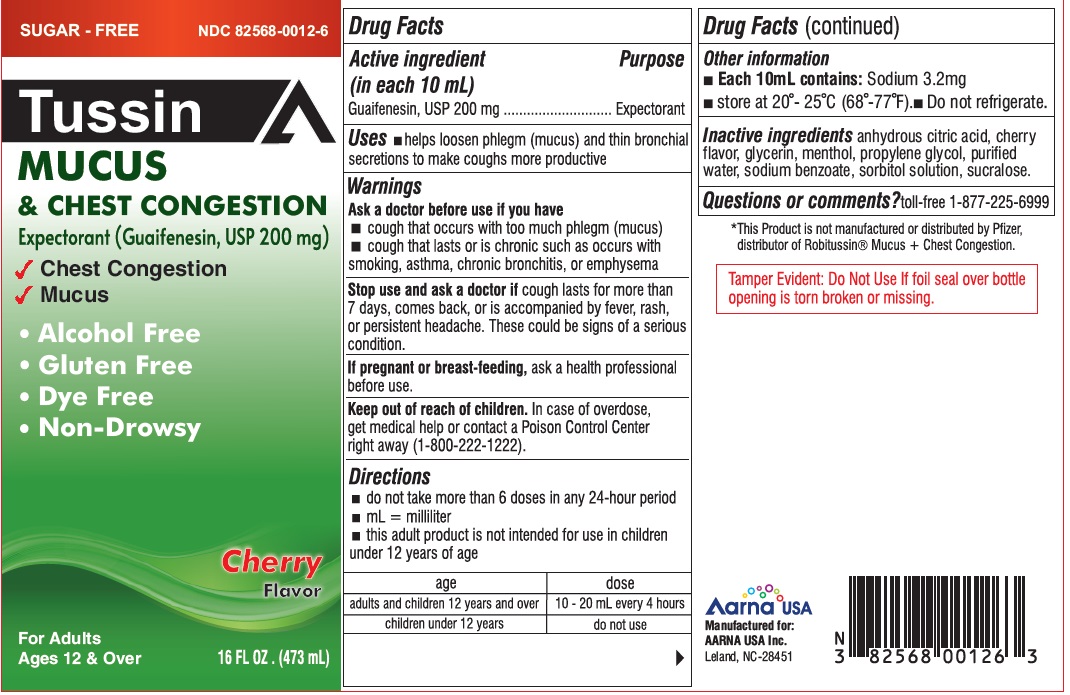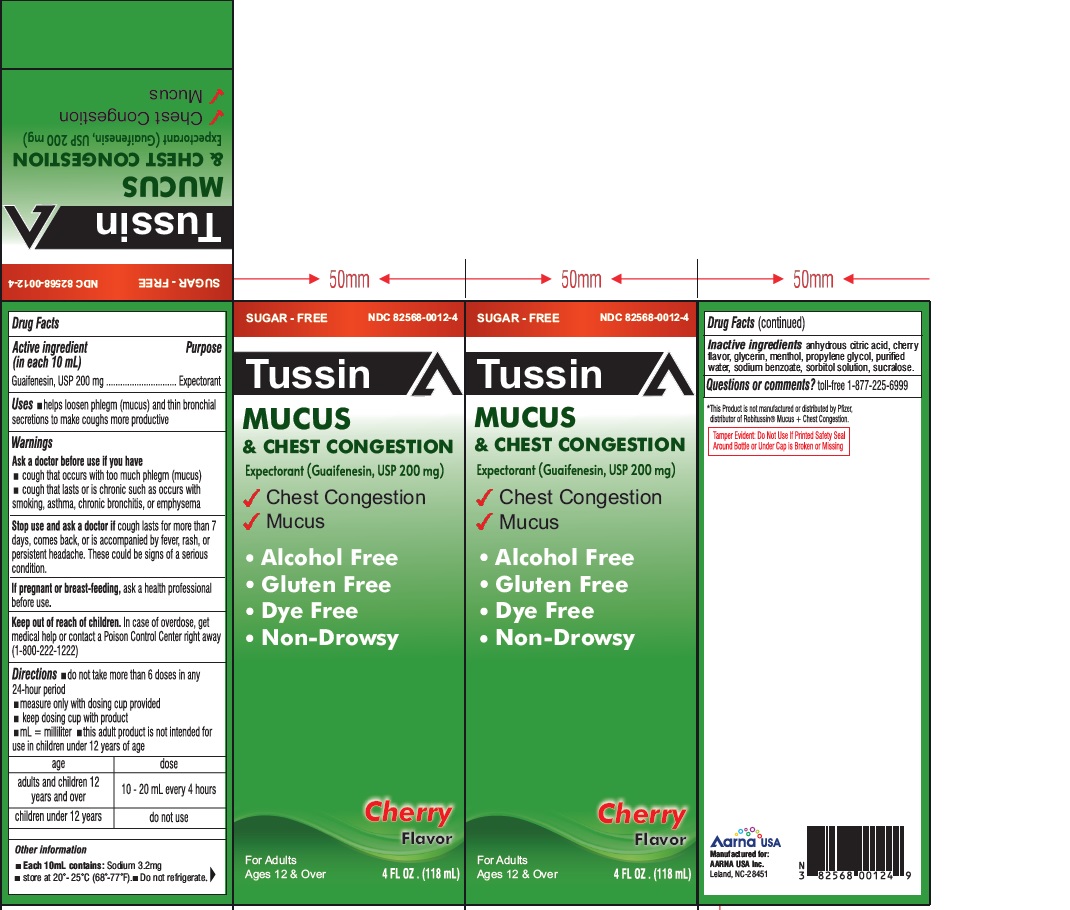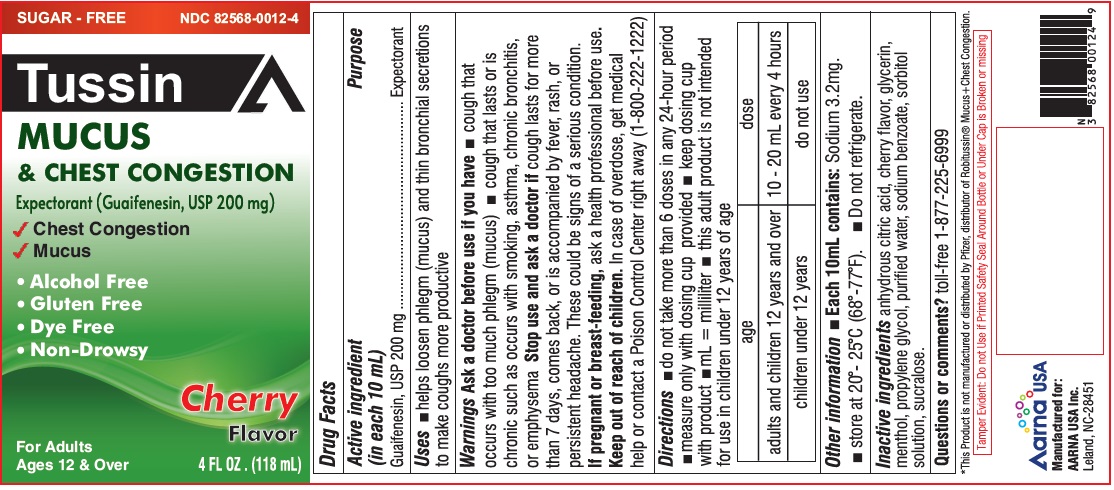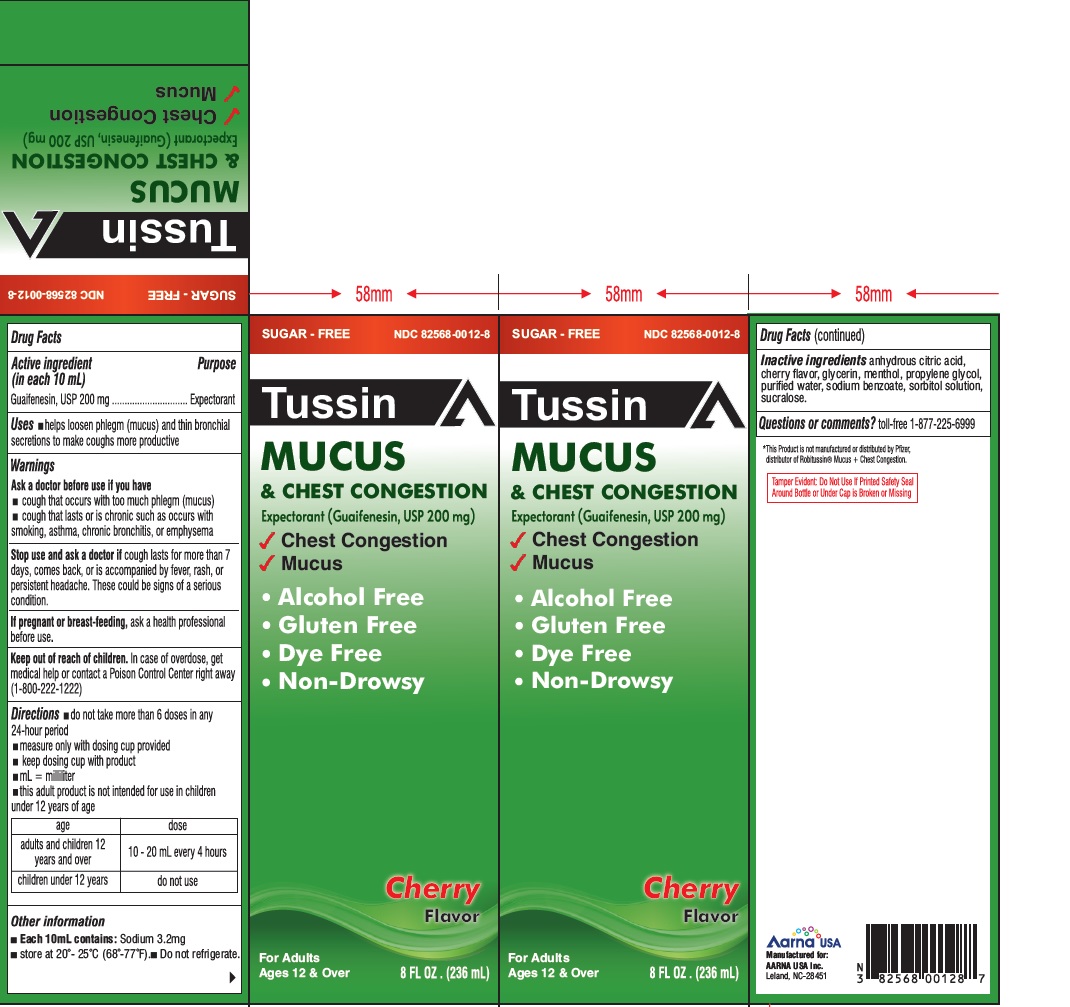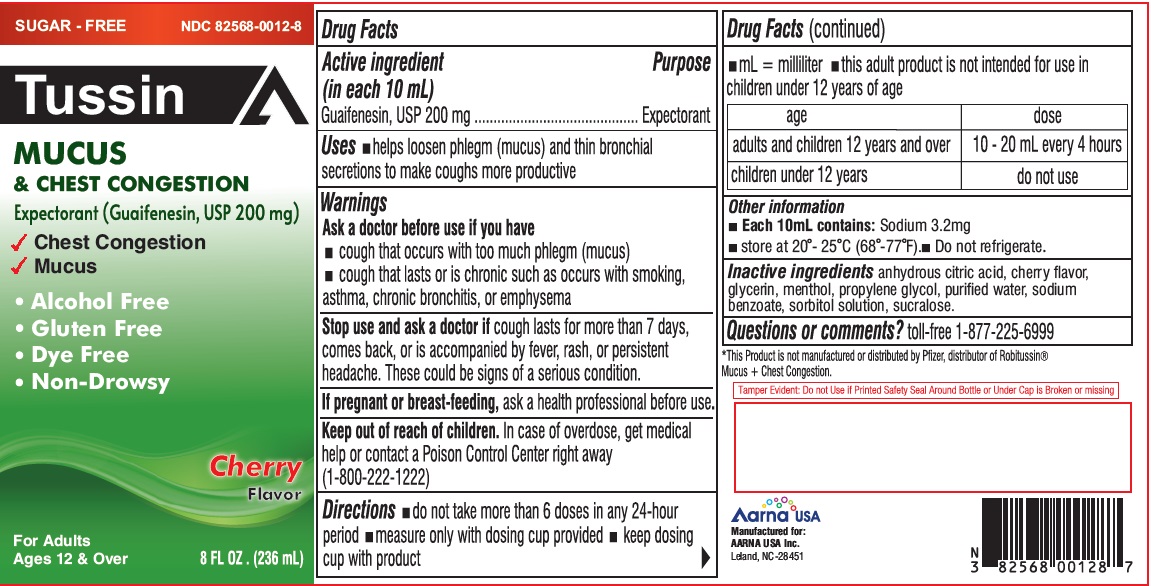 DRUG LABEL: Tussin Mucus and Chest Congestion Sugar Free
NDC: 82568-0012 | Form: LIQUID
Manufacturer: AARNA USA, Inc.
Category: otc | Type: HUMAN OTC DRUG LABEL
Date: 20230515

ACTIVE INGREDIENTS: GUAIFENESIN 200 mg/10 mL
INACTIVE INGREDIENTS: ANHYDROUS CITRIC ACID; GLYCERIN; MENTHOL; PROPYLENE GLYCOL; WATER; SODIUM BENZOATE; SORBITOL SOLUTION; SUCRALOSE

TUSSIN
Mucus and Chest Congestion
Cherry Flavor
Drug Facts

Active ingredient (in each 10 mL)

Guaifenesin, USP 200 mg

Purposes

Expectorant

Purposes

Expectorant

Uses

- helps loosen phlegm (mucus) and thin bronchial secretions to make coughs more productive

Warnings

Ask a doctor before use if you have

- cough that occurs with too much phlegm (mucus)
- cough that lasts or is chronic such as occurs with smoking, asthma, chronic bronchitis or emphysema

Stop use and ask a doctor if

cough lasts more than 7 days, comes back, or is accompanied by fever, rash, or persistent headache. These could be signs of a serious condition.

If pregnant or breast-feeding,

ask a health professional before use.

Keep out of reach of children.

In case of overdose, get medical help or contact a Poison Control Center right away (1-800-222-1222).

Directions

- do not take more than 6 doses in any 24-hour period
- mL= milliliter
- this adult product is not intended for use in children under 12 years of age

age | dose
adults and children 12 years and over | 10 - 20 mL every 4 hours
children under 12 years | do not use

Other information

- Each 10 mL contains: Sodium 3.2 mg
- store between 20º-25ºC(68º-77ºF). Do not refrigerate.

Inactive ingredients

anhydrous citric acid, cherry flavor, glycerin, menthol, propylene glycol, purified water, sodium benzoate, sorbitol solution, sucralose.

Questions or comments?

toll-free 1-877-225-6999

Manufactured for:

AARNA USA Inc.

Leland NC, 28451